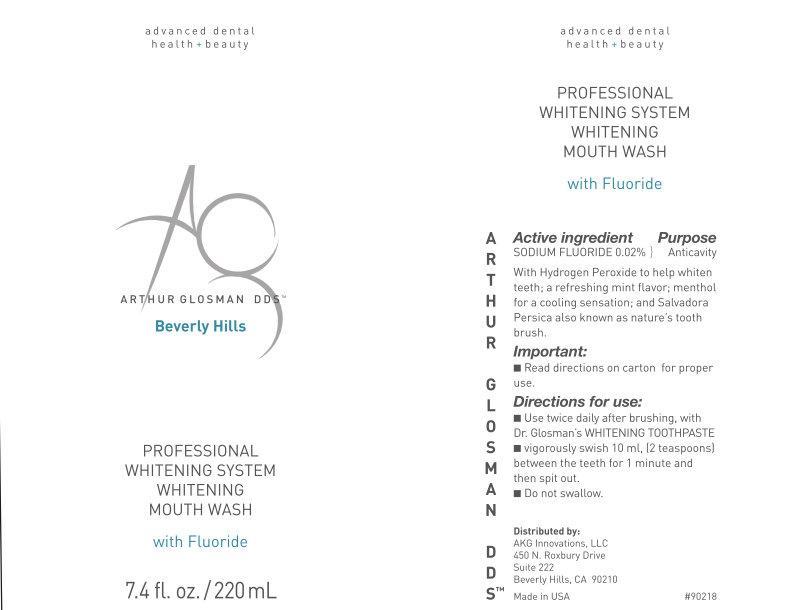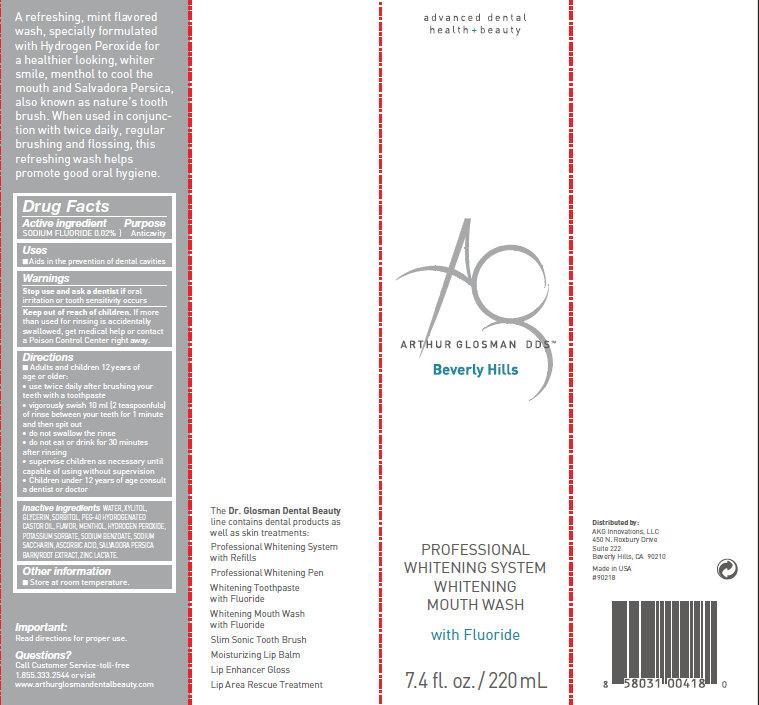 DRUG LABEL: PROFESSIONAL WHITENING SYSTEM WHITENING MOUTH WASH
NDC: 62111-0212 | Form: MOUTHWASH
Manufacturer: AKG Innovations LLC
Category: otc | Type: HUMAN OTC DRUG LABEL
Date: 20140214

ACTIVE INGREDIENTS: SODIUM FLUORIDE .2 mg/1 mL
INACTIVE INGREDIENTS: WATER; XYLITOL; GLYCERIN; SORBITOL; CASTOR OIL; MENTHOL; HYDROGEN PEROXIDE; POTASSIUM SORBATE; SODIUM BENZOATE; SACCHARIN SODIUM; ASCORBIC ACID; SALVADORA PERSICA ROOT; ZINC LACTATE

PROFESSIONAL WHITENING SYSTEM WHITENING MOUTH WASH

Drug Facts

Active ingredient

Sodium fluoride 0.02%

Purpose

Anticavity

Uses

■Aids in the prevention of dental cavities

Warnings

Stop use and ask a dentist

if oral irritation or tooth sensitivity occurs

Keep out of reach of children.

If more than used for rinsing is accidentally swallowed, get medical help or contact a Poison Control Center right away.

Directions

- Adults and children 12 years of
  age or older:
  • use twice daily after brushing your
  teeth with a toothpaste
  • vigorously swish 10 ml (2 teaspoonfuls)
  of rinse between your teeth for 1 minute
  and then spit out
  • do not swallow the rinse
  • do not eat or drink for 30 minutes
  after rinsing
  • supervise children as necessary until
  capable of using without supervision
  • Children under 12 years of age consult
  a dentist or doctor

Inactive ingredients

WATER, XYLITOL,

GLYCERIN, SORBITOL, PEG-40 HYDROGENATED

CASTOR OIL, FLAVOR, MENTHOL, HYDROGEN PEROXIDE,

POTASSIUM SORBATE, SODIUM BENZOATE, SODIUM

SACCHARIN, ASCORBIC ACID, SALVADORA PERSICA

BARK/ROOT EXTRACT, ZINC LACTATE.

Other information

■Store at room temperature.

Questions?

Call Customer Service-toll-free

1.855.333.2544 or visit

www.arthurglosmandentalbeauty.com

PROFESSIONAL WHITENING SYSTEM WHITENING MOUTH WASH with Fluoride (62111-0212-4)

advanced dental

health + beauty

Arthur Glosman DDS

Beverly Hills

PROFESSIONAL

WHITENING SYSTEM

WHITENING

MOUTH WASH

with Fluoride

7.4 fl. oz. / 220 mL

Active ingredient Purpose

SODIUM FLUORIDE 0.02% Anticavity

With Hydrogen Peroxide to help whiten

teeth; a refreshing mint flavor; menthol

for a cooling sensation; and Salvadora

Persica also known as nature’s tooth

brush.

Important:

■Read directions on carton for proper

use.

Directions for use:

■Use twice daily after brushing, with

Dr. Glosman’s WHITENING TOOTHPASTE

■vigorously swish 10 ml, (2 teaspoons)

between the teeth for 1 minute and

then spit out.

■Do not swallow.

Distributed by:

AKG Innovations, LLC

450 N. Roxbury Drive

Suite 222

Beverly Hills, CA 90210

Made in USA

A refreshing, mint flavoredwash, specially formulated with Hydrogen Peroxide for a healthier looking, whiter smile, menthol to cool the mouth and Salvadora Persica, also known as nature’s tooth brush. When used in conjunction with twice daily, regular brushing and flossing, this refreshing wash helps promote good oral hygiene.

The Dr. Glosman Dental Beauty line contains dental products as well as skin treatments:

Professional Whitening System with Refills

Professional Whitening Pen

Whitening Toothpaste with Fluoride

Whitening Mouth Wash with Fluoride

Slim Sonic Tooth Brush

Moisturizing Lip Balm

Lip Enhancer Gloss

Lip Area Rescue Treatment